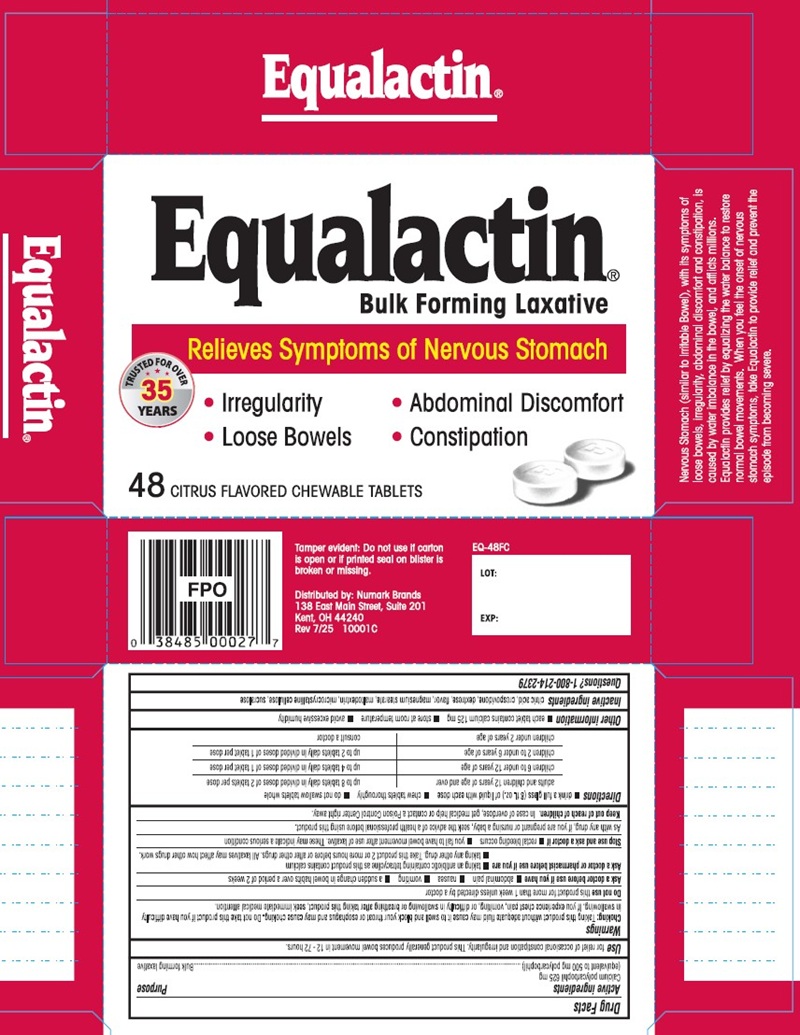 DRUG LABEL: Equalactin Laxative
NDC: 69846-000 | Form: TABLET
Manufacturer: NUMARK BRANDS, INC
Category: otc | Type: HUMAN OTC DRUG LABEL
Date: 20251203

ACTIVE INGREDIENTS: Calcium Polycarbophil 625 mg/1 1
INACTIVE INGREDIENTS: Citric Acid Monohydrate; Crospovidone; Dextrose, Unspecified Form; Magnesium Stearate; Maltodextrin; Cellulose, Microcrystalline; Sucralose

Drug Facts

Active Ingredients

Calcium polycarbophil 625 mg
(equivalent to 500 mg polycarbophil)

Purpose

Bulk for mixing Laxative

Use

for relief of occasional constipation and irregularity. This product generally produces bowel movement in 12 - 72 hours.

Warnings

Choking: Taking this product without adequate fluid may cause it to swell and block your throat or esophagus and may cause choking. Do not take this product if you have difficulty in swallowing. If you experience chest pain, vomiting, or difficulty in swallowing or breathing after taking this product, seek immediate medical attention.

Do not use

this product for more than 1 week unless directed by a doctor

Ask a doctor before use if you have

- abdominal pain
- nausea
- vomiting
- a sudden change in bowel habits over a period of 2 weeks

Ask a doctor or pharmacist before use if you are

- taking an antibiotic containing tetracycline as this product contains calcium
- taking any other drug. Take this product 2 or more hours before or after other drugs. All laxatives may affect how other drugs work.

Stop use and ask a doctor if

- rectal bleeding occurs
- you fail to have bowel movement after use of laxative. These may indicate a serious condition

PREGNANCY OR BREAST FEEDING

As with any drug, if you are pregnant or nursing a baby, seek the advice of a health professional before using this product

Keep out of reach of children. In case of overdose, get medical help or contact a Poison Control Center right away.

Directions

- drink a full glass (8 fl. oz.) of liquid with each dose
- chew tablets thoroughly
- do not swallow tablets whole

adults and children 12 years of age and over | up to 8 tablets daily in divided doses of 2 tablets per dose
children 6 to under 12 years of age | up to 4 tablets daily in divided doses of 1 tablet per dose
children 2 to under 6 years of age | up to 2 tablets daily in divided doses of 1 tablet per dose
children under 2 years of age | consult a doctor

Other information

- each tablet contains calcium 125 mg
- store at room temperature
- avoid excessive humidity

INACTIVE INGREDIENT

Inactive ingredients citric acid, crospovidone, dextrose, flavor, magnesium stearate, maltodextrin, microcrystalline cellulose, sucralose

Questions? 1-800-331-0221

PRINCIPAL DISPLAY PANEL

Equalactin®
Bulk Forming Laxative
Relieves Symptoms of Nervous Stomach

- Irregularity
- Abdominal Discomfort
- Loose Bowels
- Constipation

48 CITRUS FLAVORED CHEWABLE TABLETS
Nervous Stomach (similar to Irritable Bowel), with its symptoms of loose bowels, irregularity, abdominal discomfort and constipation, is caused by water imbalance in the bowel, and afflicts millions. Equalactin provides relief by equalizing the water balance to restore normal bowel movements. When you feel the onset of nervous stomach symptoms, take Equalactin to provide relief and prevent the episode from becoming severe.
Tamper evident: Do not use if carton
is open or if printed seal on blister is
broken or missing.
Distributed by: Numark Brands
138 East Main Street, Suite 201
Kent, OH 44240
Rev 7/25 10001C
EQ-48FC
LOT:
EXP: